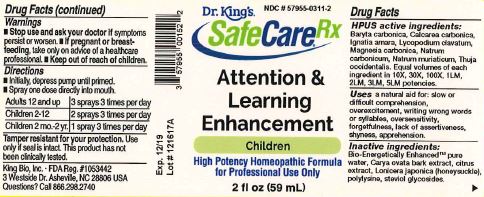 DRUG LABEL: Attention and Learning Enhancement
NDC: 57955-0311 | Form: LIQUID
Manufacturer: King Bio Inc.
Category: homeopathic | Type: HUMAN OTC DRUG LABEL
Date: 20180214

ACTIVE INGREDIENTS: BARIUM CARBONATE 10 [hp_X]/59 mL; OYSTER SHELL CALCIUM CARBONATE, CRUDE 10 [hp_X]/59 mL; STRYCHNOS IGNATII SEED 10 [hp_X]/59 mL; LYCOPODIUM CLAVATUM SPORE 10 [hp_X]/59 mL; MAGNESIUM CARBONATE 10 [hp_X]/59 mL; SODIUM CARBONATE 10 [hp_X]/59 mL; SODIUM CHLORIDE 10 [hp_X]/59 mL; THUJA OCCIDENTALIS LEAFY TWIG 10 [hp_X]/59 mL
INACTIVE INGREDIENTS: WATER; CARYA OVATA BARK; CITRUS BIOFLAVONOIDS; LONICERA JAPONICA FLOWER; POLYEPSILON-LYSINE (4000 MW); REBAUDIOSIDE A

Attention and Learning Enhancement™

ACTIVE INGREDIENT

Drug Facts__________________________________________________________________________________________________________

HPUS active ingredients: Baryta carbonica, Calcarea carbonica, Ignatia amara, Lycopodium clavatum, Magnesia carbonica, Natrum carbonicum, Natrum muriaticum, Thuja occidentalis. Equal volumes of each ingredient in 10X, 30X, 100X, 1M, LM1, LM2, LM3, potencies.

INDICATIONS AND USAGE

Uses a natural aid for: slow or difficult comprehension, overexcitement, writing wrong words or syllables, oversensitivity, forgetfulness, lack of assertiveness, shyness, apprehension.

Inactive Ingredients:

Bio-Energetically Enhanced™ pure water, Carya ovata bark extract, citrus extract, Lonicera japonica(honeysuckle, polylysine, steviol glycosides.

Warnings

- Stop use and ask your doctor if symptoms persist or worsen.
- If pregnant or breast-feeding, take only on advice of a healthcare professional.

- Keep out of reach of children.

Directions

- Initially, depress pump until primed.
- Spray one dose directly into mouth.
- Adults 12 and up: 3 sprays 3 times per day.
- Children 2-12: 2 sprays 3 times per day.
- Children 2 mo-2yr: 1 spray 3 times per day.

OTHER SAFETY INFORMATION

Tamper resistant for your protection. Use only if seal is intact. This product has not been clinically tested.

PURPOSE

Uses a natural aid for:

- slow or difficult comprehension
- over excitement
- writing wrong words or syllables
- oversensitivity
- forgetfulness
- lack of assertiveness
- shyness
- apprehension